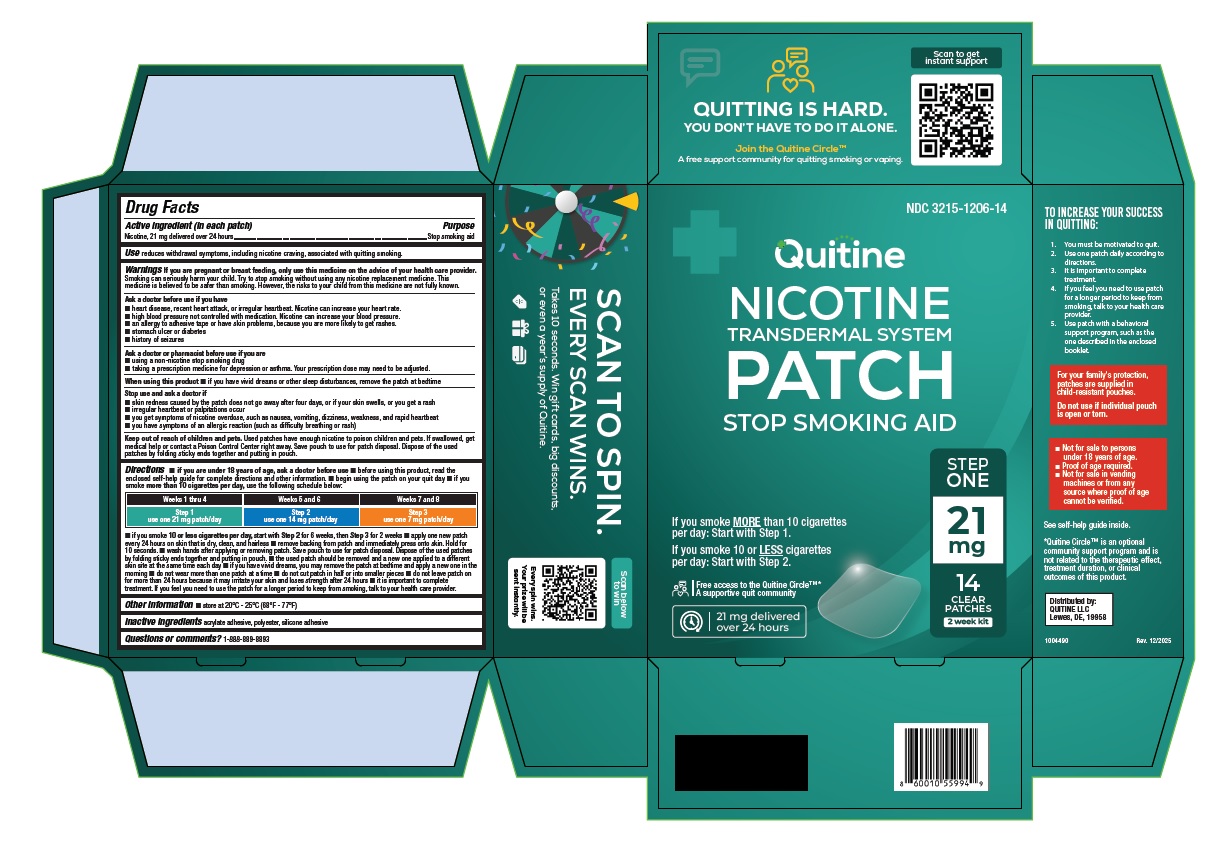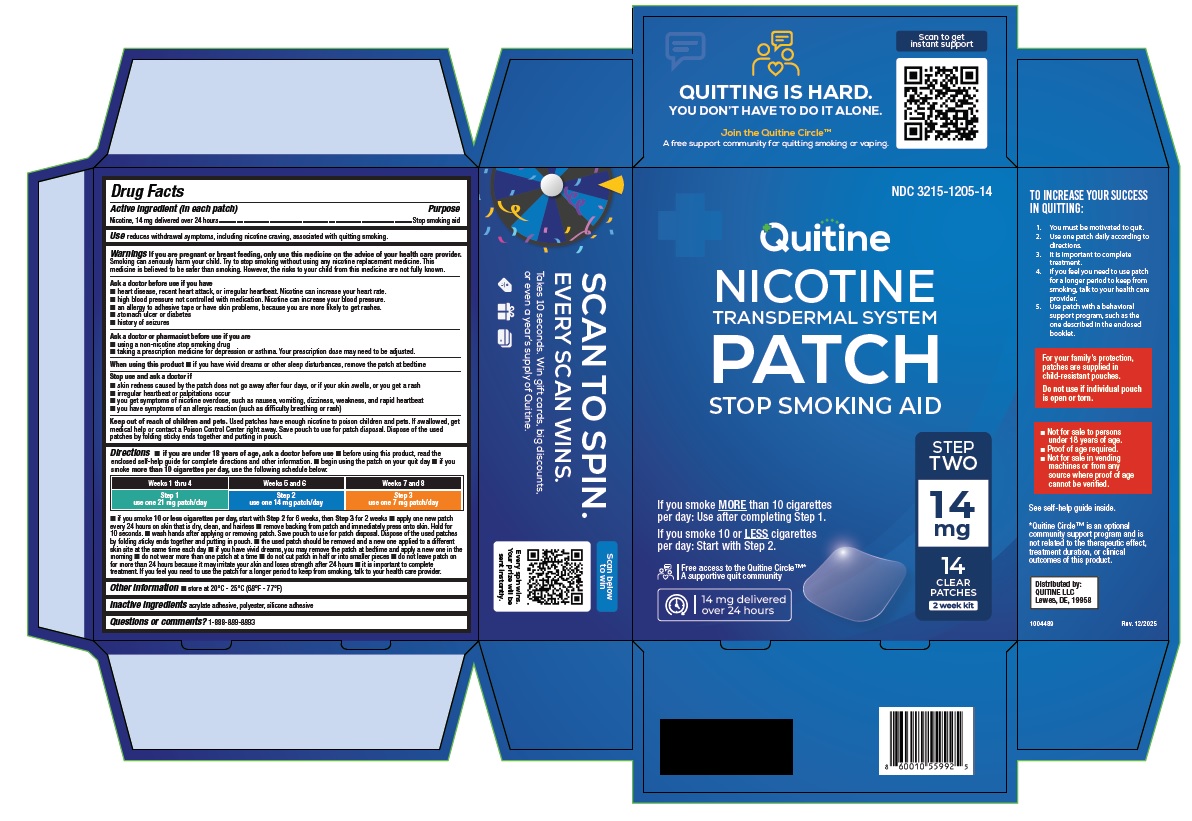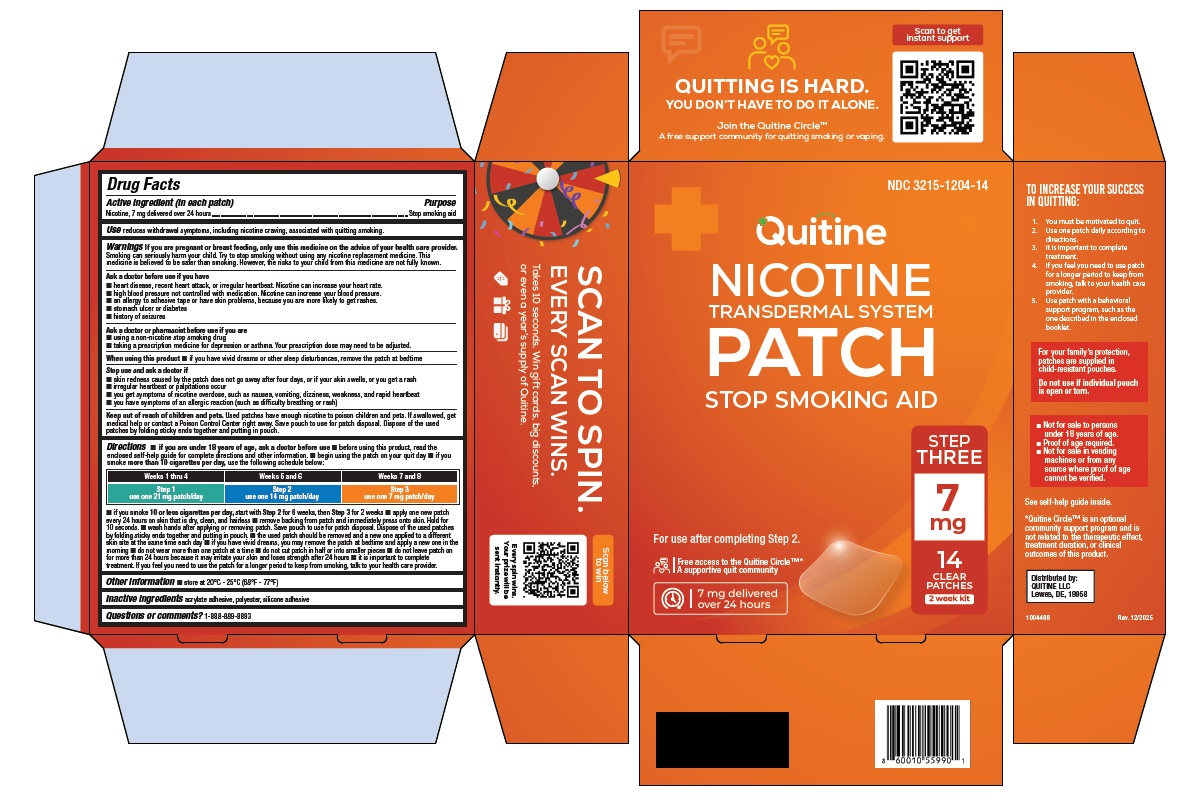 DRUG LABEL: Nicotine Transdermal System
NDC: 3215-1206 | Form: PATCH
Manufacturer: Aveva Drug Delivery Systems, Inc.
Category: otc | Type: HUMAN OTC DRUG LABEL
Date: 20260219

ACTIVE INGREDIENTS: NICOTINE 21 mg/24 h
INACTIVE INGREDIENTS: DIMETHICONE

Nicotine Transdermal System

Drug Facts

Active ingredient (in each patch)

Nicotine, 21 mg delivered over 24 hours

Active ingredient (in each patch)

Nicotine, 14 mg delivered over 24 hours

Active ingredient (in each patch)

Nicotine, 7 mg delivered over 24 hours

Purpose

Stop smoking aid

Use

reduces withdrawal symptoms, including nicotine craving, associated with quitting smoking.

Warnings

PREGNANCY OR BREAST FEEDING

If you are pregnant or breast feeding, only use this medicine on the advice of your health care provider. Smoking can seriously harm your child. Try to stop smoking without using any nicotine replacement medicine. This medicine is believed to be safer than smoking. However, the risks to your child from this medicine are not fully known.

Ask a doctor before use if you have

- heart disease, recent heart attack, or irregular heartbeat. Nicotine can increase your heart rate.
- high blood pressure not controlled with medication. Nicotine can increase your blood pressure.
- an allergy to adhesive tape or have skin problems, because you are more likely to get rashes.
- stomach ulcer or diabetes
- history of seizures

Ask a doctor or pharmacist before use if you are

- using a non-nicotine stop smoking drug
- taking a prescription medicine for depression or asthma. Your prescription dose may need to be adjusted.

When using this product

- if you have vivid dreams or other sleep disturbances, remove the patch at bedtime

Stop use and ask a doctor if

- skin redness caused by the patch does not go away after four days, or if your skin swells, or you get a rash
- irregular heartbeat or palpitations occur
- you get symptoms of nicotine overdose, such as nausea, vomiting, dizziness, weakness, and rapid heartbeat
- you have symptoms of an allergic reaction (such as difficulty breathing or rash)

Keep out of reach of children and pets.

Used patches have enough nicotine to poison children and pets. If swallowed, get medical help or contact a Poison Control Center right away. Save pouch to use for patch disposal. Dispose of the used patches by folding sticky ends together and putting in pouch.

Directions

- If you are under 18 years of age, ask a doctor before use
- before using this product, read the enclosed self-help guide for complete directions and other information.
- begin using the patch on your quit day
- if you smoke more than 10 cigarettes per day,use the following schedule below:

Weeks 1 thru 4 | Weeks 5 and 6 | Weeks 7 and 8
Step 1 | Step 2 | Step 3
use one 21 mg patch/day | use one 14 mg patch/day | use one 7 mg patch/day

- if you smoke 10 or less cigarettes per day, start with Step 2 for 6 weeks, then Step 3 for 2 weeks
- apply one new patch every 24 hours on skin that is dry, clean, and hairless
- remove backing from patch and immediately press onto skin. Hold for 10 seconds.
- wash hands after applying or removing patch. Save pouch to use for patch disposal. Dispose of the used patches by folding sticky ends together and putting in pouch.
- the used patch should be removed and a new one applied to a different skin site at the same time each day
- if you have vivid dreams, you may remove the patch at bedtime and apply a new one in the morning
- do not wear more than one patch at a time
- do not cut patch in half or into smaller pieces
- do not leave patch on for more than 24 hours because it may irritate your skin and loses strength after 24 hours
- it is important to complete treatment. If you feel you need to use the patch for a longer period to keep from smoking, talk to your health care provider.

Other information

- store at 20°C - 25°C (68°F - 77°F)

Inactive ingredients

acrylate adhesive, polyester, silicone adhesive

Questions or comments?

1-888-889-8893

TO INCREASE YOUR SUCCESS IN QUITTING:

1. You must be motivated to quit.
2. Use one patch daily according to directions.
3. It is important to complete treatment.
4. If you feel you need to use patch for a longer period to keep from smoking, talk to your health care provider.
5. Use patch with a behavioral support program, such as the one described in the enclosed booklet.

- Not for sale to persons under 18 years of age.
- Proof of age required.
- Not for sale in vending machines or from any source where proof of age cannot be verified.

For your family’s protection, patches are supplied in child-resistant pouches.

Do not use if individual pouch is open or torn.

See self-help guide inside.

*Quitine Circle™ is an optional community support program and is not related to the therapeutic effect, treatment duration, or clinical outcomes of this product.

Distributed by:
QUITINE LLC
Lewes, DE, 19958

Rev. 12/2025

PRINCIPAL DISPLAY PANEL - STEP ONE 21 mg 14 CARTON

NDC 3215-1206-14

Quitine

NICOTINE TRANSDERMAL SYSTEM PATCH

STOP SMOKING AID

STEP ONE

21 mg

14 CLEAR PATCHES

2 week kit

If you smoke MORE than 10 cigarettes per day: Start with Step 1.

If you smoke 10 or LESS cigarettes per day: Start with Step 2.

Free access to the Quitine CircleTM*

A supportive quite community

21 mg deliverd over 24 hours

PRINCIPAL DISPLAY PANEL - STEP TWO 14 mg CARTON

NDC 3215-1205-14

Quitine

NICOTINE TRANSDERMAL SYSTEM PATCH

STOP SMOKING AID

STEP TWO

14 mg

14 CLEAR PATCHES

2 week kit

If you smoke MOREthan 10 cigarettes per day: Use after completing Step 1.

If you smoke 10 or LESS cigarettes per day: Start with Step 2.

Free access to the Quitine CircleTM*

A supportive quite community

14 mg deliverd over 24 hours

PRINCIPAL DISPLAY PANEL - STEP THREE 7 mg CARTON

NDC 3215-1204-14

Quitine

NICOTINE TRANSDERMAL SYSTEM PATCH

STOP SMOKING AID

STEP THREE

7 mg

14 CLEAR PATCHES

2 week kit

For use sfter completing Step 2.

Free access to the Quitine CircleTM*

A supportive quite community

7 mg deliverd over 24 hours